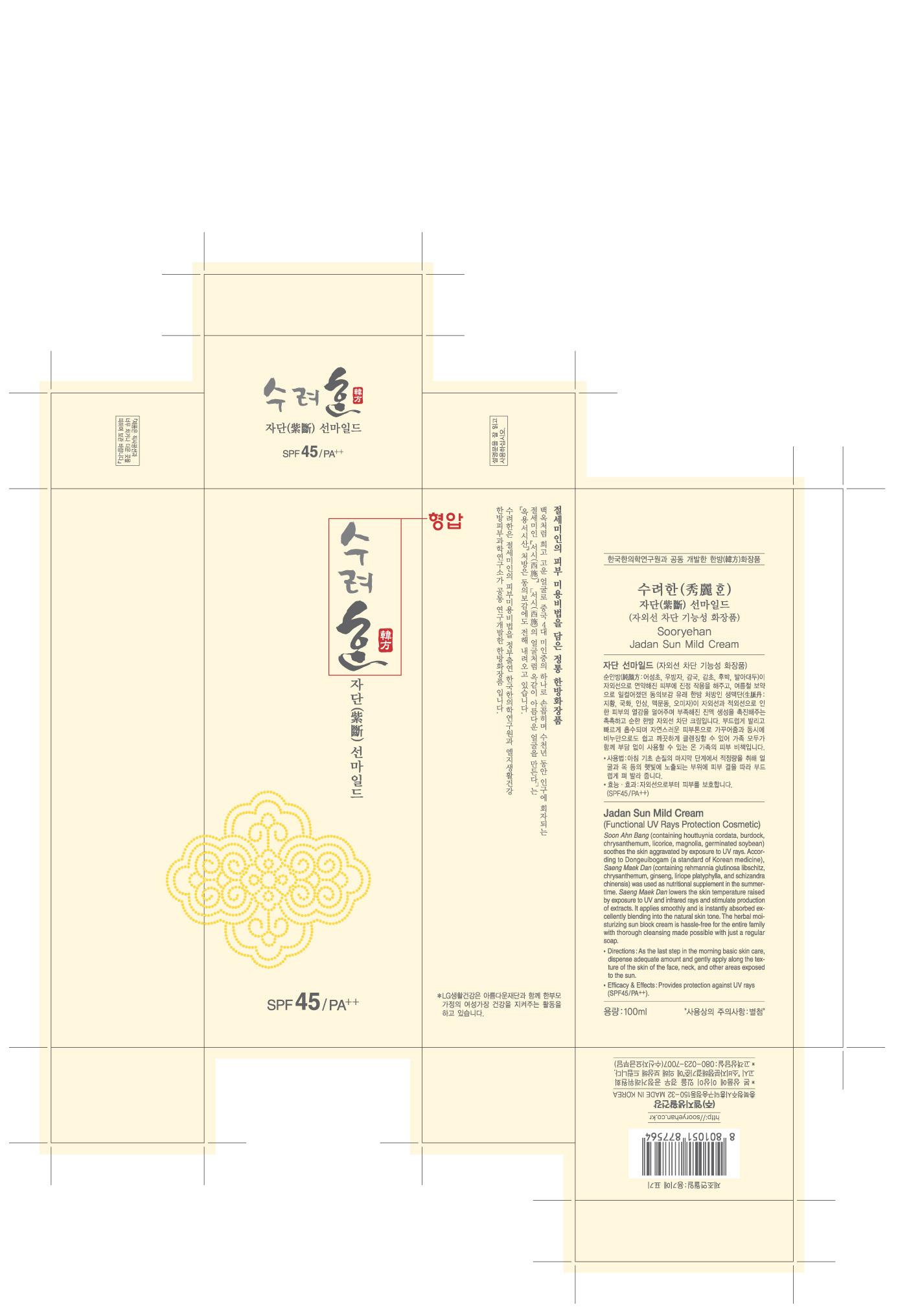 DRUG LABEL: Sooryehan Jadan Sun Mild 
NDC: 53208-446 | Form: CREAM
Manufacturer: LG Household and Healthcare, Inc.
Category: otc | Type: HUMAN OTC DRUG LABEL
Date: 20100520

ACTIVE INGREDIENTS: ZINC OXIDE 5.612 mL/100 mL; OCTINOXATE 7 mL/100 mL; TITANIUM DIOXIDE 2 mL/100 mL; OCTOCRYLENE 2 1/100 mL
INACTIVE INGREDIENTS: CYCLOMETHICONE 5; BUTYLENE GLYCOL; HEXYL LAURATE; GLYCERIN; ISOSTEARIC ACID; PANTHENOL; SODIUM CHLORIDE; SORBITAN SESQUIOLEATE; METHYLPARABEN; PROPYLPARABEN; ETHYLPARABEN; POTASSIUM HYDROXIDE

DRUG FACTS

ACTIVE INGREDIENT

ZINC OXIDE 5.612mL/100mL
OCTINOXATE 7mL/100mL
OCTOCRYLENE 2mL/100mL
TITANIUM DIOXIDE 2mL/100mL

WARNINGS AND PRECAUTIONS

For external use only.

Keep out of reach of children. Is swallowed, get medical help or contact a Poison Control Center right away.

WHEN USING

Keep out of eyes. Rinse with water to remove.

Stop use if a rash or irritation develops and lasts.

PACKAGE LABEL

Sooryehan
Sun Mild
SPF 45/PA++